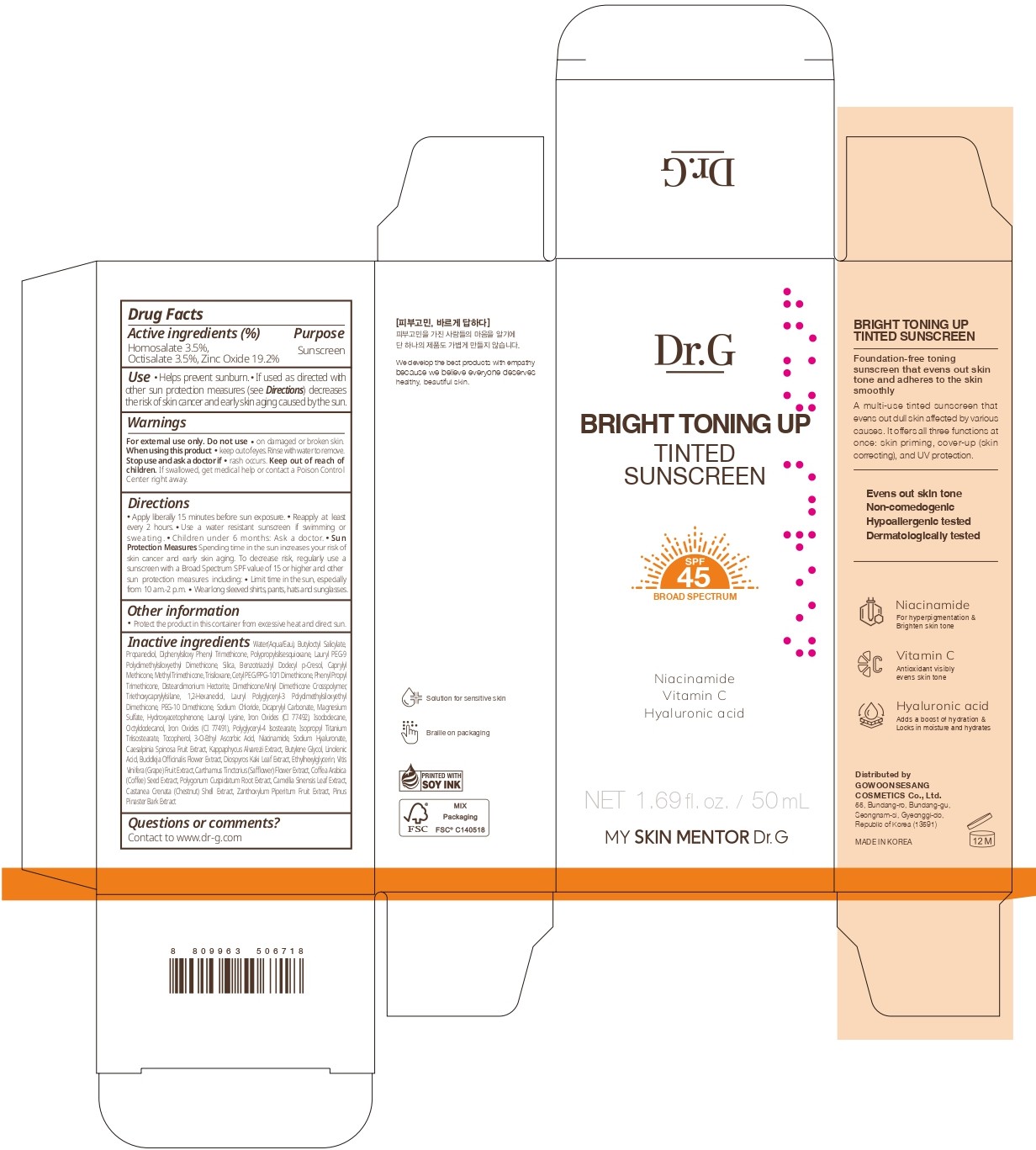 DRUG LABEL: Dr.G BRIGHT TONING UP TINTED SUNSCREEN
NDC: 51621-021 | Form: CREAM
Manufacturer: GOWOONSESANG COSMETICS CO., LTD.
Category: otc | Type: HUMAN OTC DRUG LABEL
Date: 20250320

ACTIVE INGREDIENTS: OCTISALATE 3.5 g/100 mL; HOMOSALATE 3.5 g/100 mL; ZINC OXIDE 19.2 g/100 mL
INACTIVE INGREDIENTS: SILICA; TRIETHOXYCAPRYLYLSILANE; PEG-10 DIMETHICONE (200 CST); LAUROYL LYSINE; LINOLENIC ACID; ETHYLHEXYLGLYCERIN; CARTHAMUS TINCTORIUS (SAFFLOWER) FLOWER; POLYGONUM CUSPIDATUM ROOT; TOCOPHEROL; BUDDLEJA OFFICINALIS FLOWER; CAMELLIA SINENSIS LEAF; SODIUM HYALURONATE; DIOSPYROS KAKI LEAF; CASTANEA CRENATA SHELL; MARITIME PINE; MAGNESIUM SULFATE; CI 77492; BENZOTRIAZOLYL DODECYL P-CRESOL; TRISILOXANE; TARA SPINOSA FRUIT; KAPPAPHYCUS ALVAREZII; BUTYLENE GLYCOL; ZANTHOXYLUM PIPERITUM FRUIT PULP; DICAPRYLYL CARBONATE; HYDROXYACETOPHENONE; OCTYLDODECANOL; LAURYL PEG-9 POLYDIMETHYLSILOXYETHYL DIMETHICONE; DISTEARDIMONIUM HECTORITE; WATER; DIPHENYLSILOXY PHENYL TRIMETHICONE; METHYL TRIMETHICONE; VITIS VINIFERA (GRAPE); ARABICA COFFEE BEAN; CI 77491; POLYGLYCERYL-4 ISOSTEARATE; 1,2-HEXANEDIOL; ISOPROPYL TITANIUM TRIISOSTEARATE; 3-O-ETHYL ASCORBIC ACID; NIACINAMIDE; CAPRYLYL METHICONE; BUTYLOCTYL SALICYLATE; PROPANEDIOL; SODIUM CHLORIDE; ISODODECANE

Active ingredients

Homosalate 3.5%,
Octisalate 3.5%, Zinc Oxide 19.2%

Purpose

Sunscreen

Use

- Helps prevent sunbum.
- If used as directed with other sun protection measures (see Directions) decreases the risk of skin cancer and early skin aging caused by the sun.

Warnings

For external use only. Do not use

- on damaged or broken skin.

When using this product

- keep out of eyes. Rinse with water to remove.

Stop use and ask a doctor if

- rash occurs.

Keep out of reach of children.

If swallowed, get medical help or contact a Poison Control Center right away.

Directions

- Apply liberally 15 minutes before sun exposure.
- Reapply at least every 2 hours.
- Use a water resistant sunscreen if swimming or sweating.
- Children under 6 months: Ask a doctor.
- Sun Protection Measures Spending time in the sun increases your risk of skin cancer and early skin aging. To decrease risk, regularly use a sunscreen with a Broad Spectrum SPF value of 15 or higher and other sun protection measures including:
- Limit time in the sun, especially from 10 am .- 2 p.m.
- Wear long sleeved shirts, pants, hats and sunglasses.

Other information

- Protect the product in this container from excessive heat and direct sun.

Inactive ingredients

Water(Aqqua/Eau), Butyloctyl Salicylate, Propanediol, Diphenylsiloxy Phenyl Trimethicone, Polypropylsilsesquioxane, Lauryl PEG-9
Polydimethylsiloxyethyl Dimethicone, Silica, Benzotriazolyl Dodecyl p-Cresol, Capryiyl Methicone, Methyl Trimethicone, Trisiloxane, Cetyl PEG/PPG-10/1 Dimethicone, Phenyl Propyl Trimethicone, Disteardimonium Hectorite, Dimethicone/inyl Dimethicone Crosspolymer, Triethoxycaprylylsilane, 1,2-Hexanediol, Lauryl Polyglyceryl-3 Polydimethylsiloxyethyl Dimethicone, PEG-10 Dimethicone, Sodium Chloride, Dicaprylyl Carbonate, Magnesium Sulfate, Hydroxyacetophenone, Lauroyl Lysine, Iron Oxides (CI 77492), Isododecane, Octyldodecanol, iron Oxides (C 77491), Polyglyceryl-4 Isostearate, Isopropyl Titanium Triisostearate, Tocopherol, 3-0-Ethyl Ascorbic Acid, Niacinamide, Sodium Hyaluronate, Caesalpinia Spinosa Fruit Extract, Kappaphycus Alvarezi Extract, Butylene Glycol, Linolenic Acid, Buddleja Officinalis Flower Extract, Diospyros Kaki Leaf Extract, Ethylhexylglycerin, Vitis
Vinifera (Grape) Fruit Extract, Carthamus Tinctorius (Safflower) Flower Extract, Coffea Arabica (Coffee) Seed Extract, Polygonum Cuspidatum Root Extract, Camelia Sinensis Leaf Extract, Castanea Crenata (Chestnut) Shell Extract, Zanthoxylum Piperitum Fruit Extract, Pinus Pinaster Bark Extract

Questions or comments?

Contact to www.dr-g.com